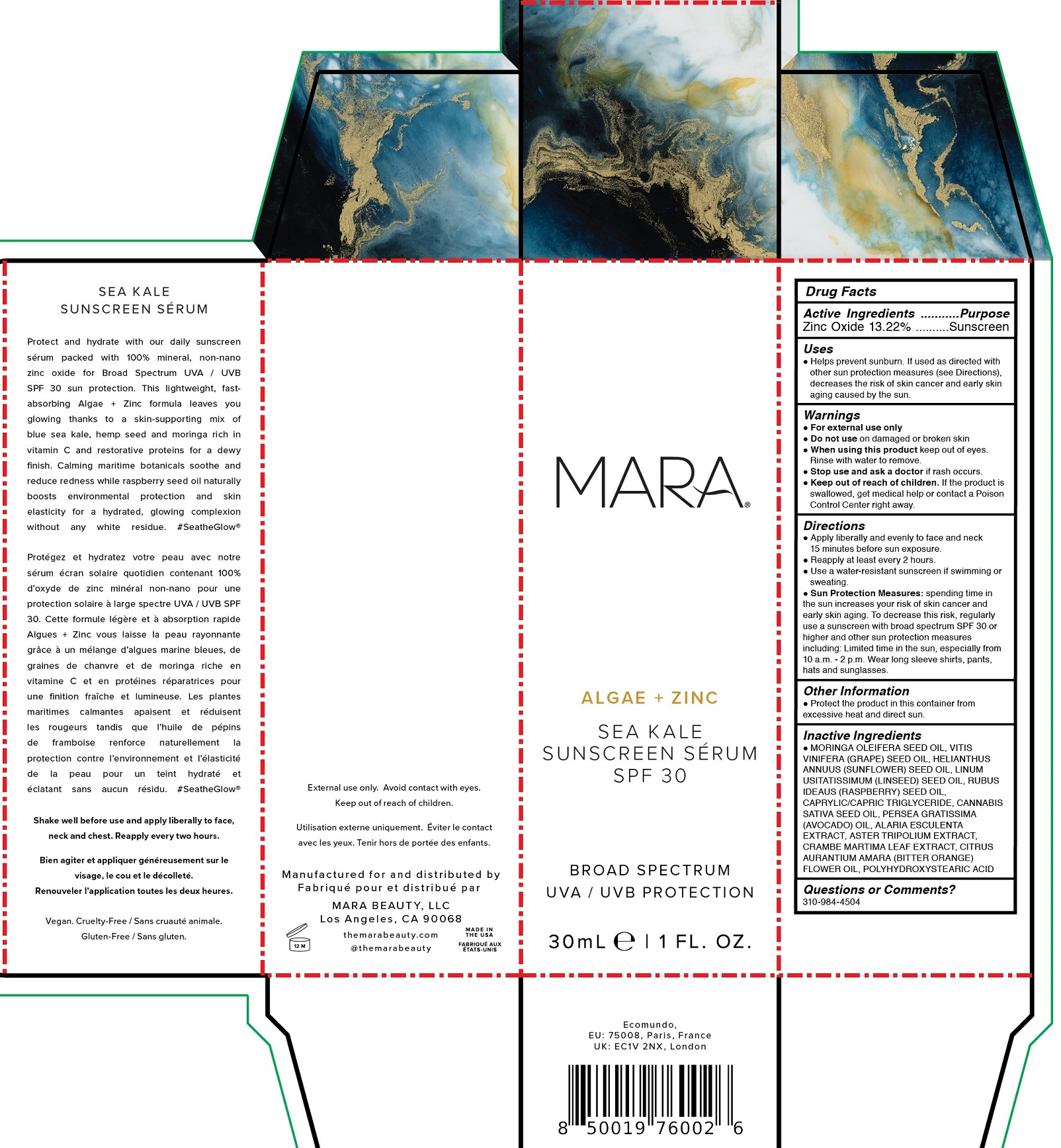 DRUG LABEL: MARA Algae Zinc Sea Kale Sunscreen Serum SPF 30
NDC: 81461-001 | Form: OIL
Manufacturer: Mara Beauty LLC
Category: otc | Type: HUMAN OTC DRUG LABEL
Date: 20231019

ACTIVE INGREDIENTS: ZINC OXIDE 132.2 mg/1 mL
INACTIVE INGREDIENTS: MORINGA OLEIFERA SEED OIL; GRAPE SEED OIL; SUNFLOWER OIL; LINSEED OIL; RASPBERRY SEED OIL; MEDIUM-CHAIN TRIGLYCERIDES; CANNABIS SATIVA SEED OIL; AVOCADO OIL; ALARIA ESCULENTA; CRAMBE MARITIMA LEAF; CITRUS AURANTIUM FLOWER OIL

MARA Algae + Zinc Sea Kale Sunscreen Serum SPF 30

Active Ingredients

Zinc Oxide 13.22%

Purpose

Sunscreen

Uses

- Helps prevent sunburn. If used as directed with other sun protection measures (see Directions), decreases the risk of skin cancer and early skin aging caused by the sun.

Warnings

- For external use only

Do not use

- on damaged or brokes skin

When using this product

- keep out of eyes. Rinse with water to remove.

Stop use and ask a doctor

- if rash occurs.

Keep out of reach of children.

- If the product is swallowed, get medical help or contact a Poison Control Center right away.

Directions

- Apply liberally and evenly to face and neck 15 minutes before sun exposure.
- Reapply at least every 2 hours.
- Use a water-resistant sunscreen if swimming or sweating.
- spending time in the sun increases your risk of skin cancer and early skin aging. To decrease this risk, regularly use a sunscreen with broad spectrum SPF 30 or higher and other sun protection measures including: Limited time in the sun, especially from 10 a.m. - 2 p.m. Wear long sleeve shirts, pants, hats and sunglasses. Sun Protection Measures:

Other Information

- Protect the product in this container from excessive heat and direct sun.

Inactive Ingredients

- MORINGA OLEIFERA SEED OIL, VITIS VINIFERA (GRAPE) SEED OIL, HELIANTHUS ANNUUS (SUNFLOWER) SEED OIL, LINUM USITATISSIMUM (LINSEED) SEED OIL, RUBUS IDAEUS (RASPBERRY) SEED OIL, CAPRYLIC/CAPRIC TRIGLYCERIDE, CANNABIS SATIVA SEED OIL, PERSEA GRATISSIMA (AVOCADO) OIL, ALARIA ESCULENTA EXTRACT, ASTER TRIPOLIUM EXTRACT, CRAMBE MARITIMA LEAF EXTRACT, CITRUS AURANTIUM AMARA (BITTER ORANGE) FLOWER OIL, POLYHYDROXYSTEARIC ACID

Questions or Comments?

310-984-4504